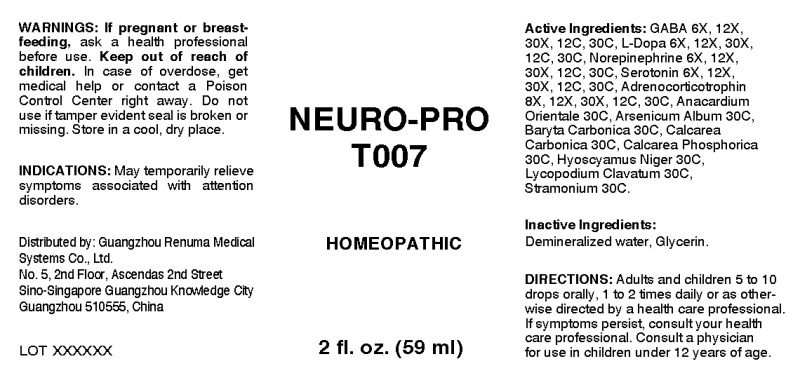 DRUG LABEL: Neuro-Pro
NDC: 71742-0001 | Form: LIQUID
Manufacturer: Guangzhou Renuma Medical Systems Co., Ltd
Category: homeopathic | Type: HUMAN OTC DRUG LABEL
Date: 20171018

ACTIVE INGREDIENTS: .GAMMA.-AMINOBUTYRIC ACID 6 [hp_X]/1 mL; LEVODOPA 6 [hp_X]/1 mL; NOREPINEPHRINE 6 [hp_X]/1 mL; SEROTONIN HYDROCHLORIDE 6 [hp_X]/1 mL; CORTICOTROPIN 8 [hp_X]/1 mL; ANACARDIUM OCCIDENTALE FRUIT 30 [hp_C]/1 mL; ARSENIC TRIOXIDE 30 [hp_C]/1 mL; BARIUM CARBONATE 30 [hp_C]/1 mL; OYSTER SHELL CALCIUM CARBONATE, CRUDE 30 [hp_C]/1 mL; TRIBASIC CALCIUM PHOSPHATE 30 [hp_C]/1 mL; HYOSCYAMUS NIGER 30 [hp_C]/1 mL; LYCOPODIUM CLAVATUM SPORE 30 [hp_C]/1 mL; DATURA STRAMONIUM 30 [hp_C]/1 mL
INACTIVE INGREDIENTS: WATER; GLYCERIN

Drug Facts:

ACTIVE INGREDIENTS:

Gaba (Gamma-Aminobutyric Acid) 6X, 12X, 30X, 12C, 30C, L-Dopa 6X, 12X, 30X, 12C, 30C, Norepinephrine 6X, 12X, 30C, 12C, 30C, Serotonin (Hydrochloride) 6X, 12X, 30X, 12C, 30C, Adrenocorticotrophin 8X, 12X, 30X, 12C, 30C, Anacardium Orientale 30C, Arsenicum Album 30C, Baryta Carbonica 30C, Calcarea Carbonica 30C, Calcarea Phosphorica 30C, Hyoscyamus Niger 30C, Lycopodium Clavatum 30C, Stramonium 30C.

INDICATIONS:

May temporarily relieve symptoms associated with attention disorders.

WARNINGS:

If pregnant or breast-feeding, ask a health care professional before use.

Keep out of reach of children. In case of overdose, get medical help or contact a Poison Control Center right away.

Do not use if tamper evident seal is broken or missing.

Store in cool, dry place.

Keep out of reach of children. In case of overdose, get medical help or contact a Poison Control Center right away.

DIRECTIONS:

Adults and children 5 to 10 drops orally, 1 to 2 times daily or as otherwise directed by a health care professional. If symptoms persist, consult your health care professional. Consult a physician for use in children under 12 years of age.

INDICATIONS:

May temporarily relieve symptoms associated with attention disorders.

INACTIVE INGREDIENTS:

Demineralized water, Glycerin

QUESTIONS:

Distributed by:

Guangzhou Renuma Medical

Systems Co., Ltd.

No. 5, 2nd Floor, Ascendas 2nd Street

Sino-Singapore Guangzhou Knowledge City

Guangzhou 510555, China

PACKAGE LABEL DISPLAY:

NEURO-PRO

T007

HOMEOPATHIC

2 fl. oz. (59 ml)